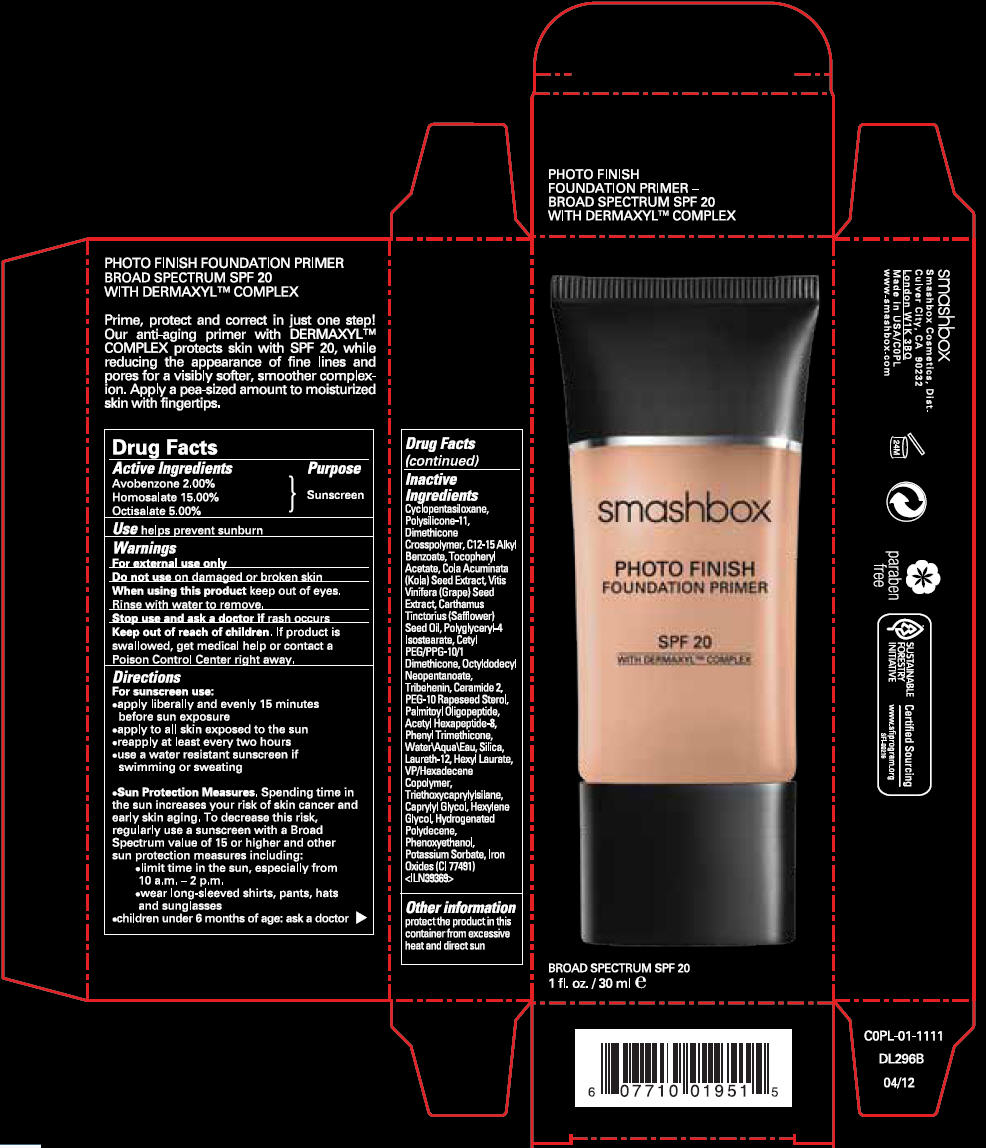 DRUG LABEL: SMASHBOX 
NDC: 10348-006 | Form: LIQUID
Manufacturer: SMASHBOX  BEAUTY COSMETICS, INC
Category: otc | Type: HUMAN OTC DRUG LABEL
Date: 20120731

ACTIVE INGREDIENTS: AVOBENZONE 2 mL/100 mL; HOMOSALATE 15 mL/100 mL; OCTISALATE 5 mL/100 mL
INACTIVE INGREDIENTS: Cyclomethicone 5; Alkyl (C12-15) Benzoate; .Alpha.-Tocopherol Acetate; cola acuminata seed; Vitis Vinifera Seed; Safflower Oil; Polyglyceryl-4 Isostearate; Octyldodecyl Neopentanoate; Tribehenin; Ceramide 2; PEG-10 Rapeseed Sterol; Palmitoyl Oligopeptide; Acetyl Hexapeptide-8; Phenyl Trimethicone; Water; Silicon Dioxide; Laureth-12; Hexyl Laurate; Triethoxycaprylylsilane; Caprylyl Glycol; Hexylene Glycol; Phenoxyethanol; Potassium Sorbate; Ferric Oxide Red

SMASHBOX PHOTO FINISH FOUNDATION PRIMER SPF 20

Drug Facts

Active Ingredients

Avobenzone 2.00%
Homosalate 15.00%
Octisalate 5.00%

Purpose

Sunscreen

Use

helps prevent sunburn

Warnings

For external use only

Do not use on damaged or broken skin

When using this product keep out of eyes. Rinse with water to remove.

Stop use and ask a doctor if rash occurs

Keep out of reach of children. If product is swallowed, get medical help or contact a Poison Control Center right away.

Directions

For sunscreen use:

- apply liberally and evenly 15 minutes before sun exposure
- apply to all skin exposed to the sun
- reapply at least every two hours
- use a water resistant sunscreen if swimming or sweating

- Sun Protection Measures. Spending time in the sun increases your risk of skin cancer and early skin aging. To decrease this risk, regularly use a sunscreen with a Broad Spectrum value of 15 or higher and other sun protection measures including:
  - limit time in the sun, especially from 10 a.m. – 2 p.m.
  - wear long-sleeved shirts, pants, hats and sunglasses
- children under 6 months of age: ask a doctor

Inactive Ingredients

Cyclopentasiloxane, Polysilicone-11, Dimethicone Crosspolymer, C12-15 Alkyl Benzoate, Tocopheryl Acetate, Cola Acuminata (Kola) Seed Extract, Vitis Vinifera (Grape) Seed Extract, Carthamus Tinctorius (Safflower) Seed Oil, Polyglyceryl-4 Isostearate, Cetyl PEG/PPG-10/1 Dimethicone, Octyldodecyl Neopentanoate, Tribehenin, Ceramide 2, PEG-10 Rapeseed Sterol, Palmitoyl Oligopeptide, Acetyl Hexapeptide-8, Phenyl Trimethicone, Water\Aqua\Eau, Silica, Laureth-12, Hexyl Laurate, VP/Hexadecene Copolymer, Triethoxycaprylylsilane, Caprylyl Glycol, Hexylene Glycol, Hydrogenated Polydecene, Phenoxyethanol, Potassium Sorbate, Iron Oxides (CI 77491) <ILN39369>

Other information

protect the product in this container from excessive heat and direct sun

Smashbox Cosmetics, Dist.
Culver City, CA 90232

PRINCIPAL DISPLAY PANEL - 30 ml Tube Carton

smashbox

PHOTO FINISH
FOUNDATION PRIMER

SPF 20
WITH DERMAXYL™ COMPLEX

BROAD SPECTRUM SPF 20
1 fl. oz. / 30 ml e